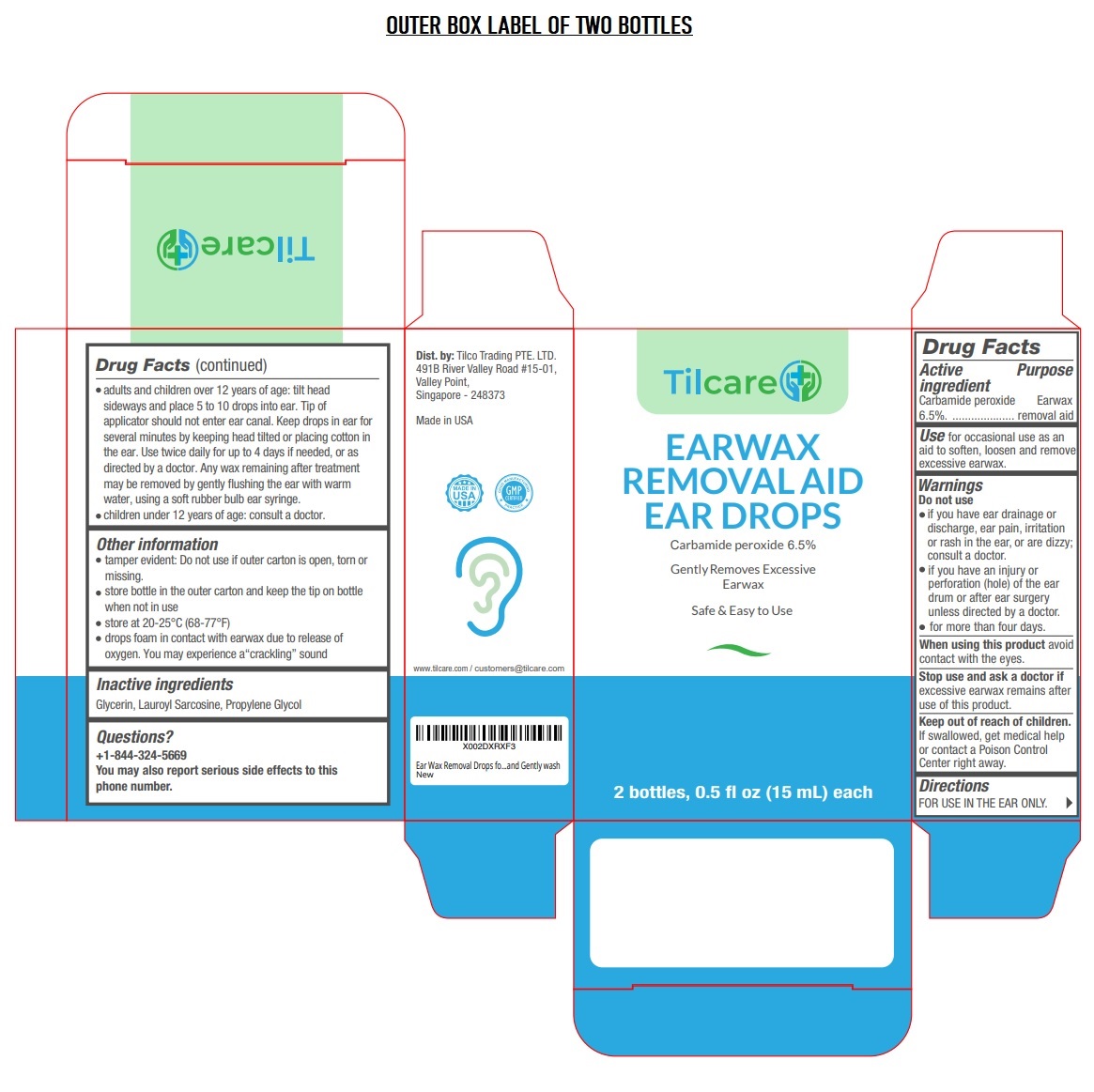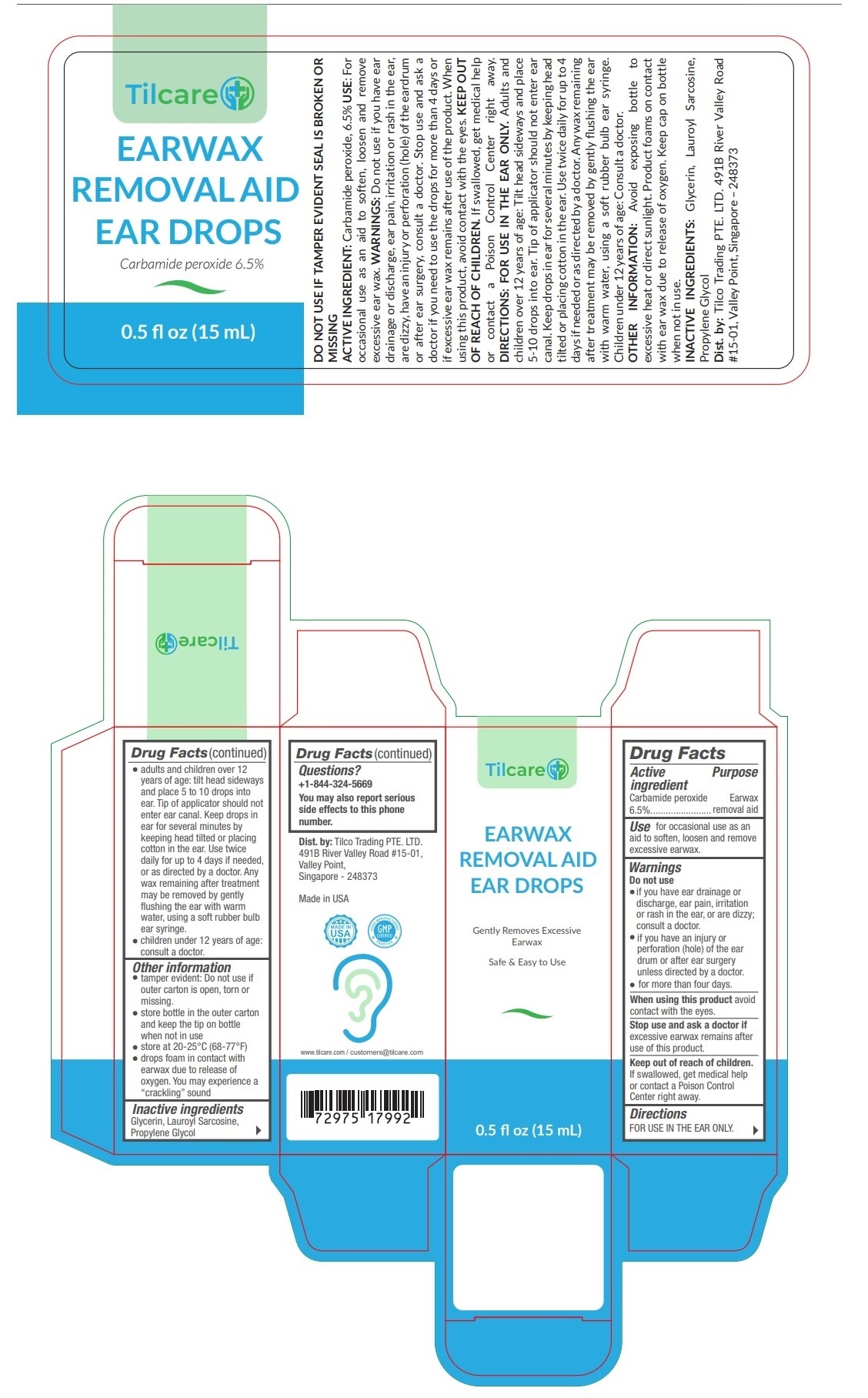 DRUG LABEL: Tilcare
NDC: 73390-101 | Form: SOLUTION/ DROPS
Manufacturer: Tilco Trading Pte. Ltd.
Category: otc | Type: HUMAN OTC DRUG LABEL
Date: 20210125

ACTIVE INGREDIENTS: CARBAMIDE PEROXIDE 6.5 g/100 mL
INACTIVE INGREDIENTS: GLYCERIN; LAUROYL SARCOSINE; PROPYLENE GLYCOL

Tilcare EARWAX REMOVAL AID EAR DROPS

Active ingredient

Carbamide peroxide 6.5%

Purpose

Earwax removal aid

Use

for occasional use as an aid to soften, loosen and remove excessive earwax.

Warnings

Do not use

• if you have ear drainage or discharge, ear pain, irritation or rash in the ear, or are dizzy; consult a doctor.

• if you have an injury or perforation (hole) of the ear drum or after ear surgery unless directed by a doctor.

• for more than four days.

When using this product avoid contact with the eyes.

Stop use and ask a doctor if excessive earwax remains after use of this product.

Keep out of reach of children. If swallowed, get medical help or contact a Poison Control Center right away.

Directions

FOR USE IN THE EAR ONLY.

• adults and children over 12 years of age: tilt head sideways and place 5 to 10 drops into ear. Tip of applicator should not enter ear canal. Keep drops in ear for several minutes by keeping head tilted or placing cotton in the ear. Use twice daily for up to 4 days if needed, or as directed by a doctor. Any wax remaining after treatment may be removed by gently ﬂushing the ear with warm water, using a soft rubber bulb ear syringe.

• children under 12 years of age: consult a doctor.

Other information

• tamper evident: Do not use if outer carton is open, torn or missing.

• store bottle in the outer carton and keep the tip on bottle when not in use

• store at 20-25°C (68-77°F)

• drops foam in contact with earwax due to release of oxygen. You may experience a “crackling” sound

Inactive ingredients

Glycerin, Lauroyl Sarcosine, Propylene Glycol

Questions?

+1-844-324-5669

You may also report serious side effects to this phone number.

Gently Removes Excessive Earwax

Safe & Easy to Use

Dist. by: Tilco Trading PTE. LTD. 491B River Valley Road #15-01, Valley Point, Singapore - 248373
Made in USA
www.tilcare.com / customers@tilcare.com

Carbamide peroxide 6.5%